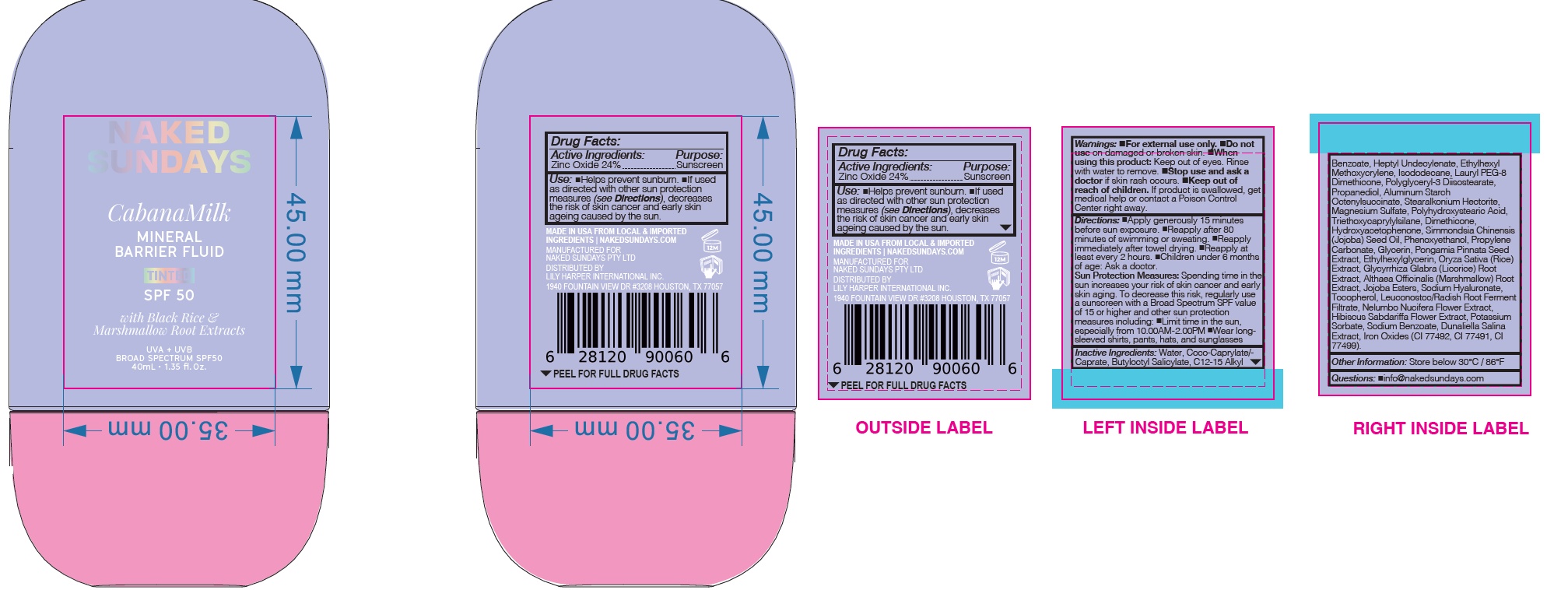 DRUG LABEL: CabanaMilk Mineral Barrier Fluid
NDC: 81104-593 | Form: LOTION
Manufacturer: NAKED SUNDAYS PTY LTD
Category: otc | Type: HUMAN OTC DRUG LABEL
Date: 20260107

ACTIVE INGREDIENTS: ZINC OXIDE 24 g/100 mL
INACTIVE INGREDIENTS: POLYGLYCERYL-3 DIISOSTEARATE; CI 77492; PROPANEDIOL; STEARALKONIUM HECTORITE; LEUCONOSTOC/RADISH ROOT FERMENT FILTRATE; GLYCERIN; ETHYLHEXYLGLYCERIN; SODIUM HYALURONATE; CI 77499; WATER; COCO-CAPRYLATE/CAPRATE; TRIETHOXYCAPRYLYLSILANE; HYDROXYACETOPHENONE; PHENOXYETHANOL; PROPYLENE CARBONATE; ALTHAEA OFFICINALIS ROOT; HYDROLYZED JOJOBA ESTERS; POTASSIUM SORBATE; DUNALIELLA SALINA; ALUMINUM STARCH OCTENYLSUCCINATE; MAGNESIUM SULFATE; HEPTYL UNDECYLENATE; ORYZA SATIVA (RICE) GERM POWDER; POLYHYDROXYSTEARIC ACID (2300 MW); C12-15 ALKYL BENZOATE; ISODODECANE; SIMMONDSIA CHINENSIS (JOJOBA) SEED OIL; BUTYLOCTYL SALICYLATE; LAURYL PEG-8 DIMETHICONE (300 CPS); CI 77491; NELUMBO NUCIFERA FLOWER; DIMETHICONE; PONGAMIA PINNATA SEED; ETHYLHEXYL METHOXYCRYLENE; GLYCYRRHIZA GLABRA (LICORICE) ROOT; HIBISCUS SABDARIFFA FLOWER; SODIUM BENZOATE

CabanaMilk Mineral Barrier Fluid

Use:

• Helps prevent sunburn.

• If used as directed with other sun protection measures (see Directions), decreases the risk of skin cancer and early skin ageing caused by the sun

Active Ingredient: Zinc Oxide 24%

PURPOSE

Sunscreen

Warnings: For external use only.

• Do not use on damaged or broken skin.

When using this product: Keep out of eyes. Rinse with water to remove.

Stop use and ask a doctor: If rash occurs.

Keep out of reach of children: If product is swallowed, get medical help or contact a Poison Control Center right away

INACTIVE INGREDIENT

Inactive Ingredients: Water, Coco-Caprylate/Caprate, Butyloctyl Salicylate, C12-15 Alkyl Benzoate, Heptyl Undecylenate, Ethylhexyl Methoxycrylene, Isododecane, Lauryl PEG-8 Dimethicone, Polyglyceryl-3 Diisostearate, Propanediol, Aluminum Starch Octenylsuccinate, Stearalkonium Hectorite, Magnesium Sulfate, Polyhydroxystearic Acid, Triethoxycaprylylsilane, Dimethicone, Hydroxyacetophenone, Simmondsia Chinensis (Jojoba) Seed Oil, Phenoxyethanol, Propylene Carbonate, Glycerin, Pongamia Pinnata Seed Extract, Ethylhexylglycerin, Oryza Sativa (Rice) Extract, Glycyrrhiza Glabra (Licorice) Root Extract, Althaea Officinalis (Marshmallow) Root Extract, Jojoba Esters, Sodium Hyaluronate, Tocopherol, Leuconostoc/Radish Root Ferment Filtrate, Nelumbo Nucifera Flower Extract, Hibiscus Sabdariffa Flower Extract, Potassium Sorbate, Sodium Benzoate, Dunaliella Salina Extract, Iron Oxides (CI 77492, CI 77491, CI 77499).

Directions:

• Shake well before use.

• Apply liberally and evenly 15 minutes before sun exposure.

• Re-apply every 2 hours or immediately after swimming, sweating or towel drying.

• Use a water-resistant sunscreen if swimming or sweating.

Children under 6 months of age: Ask a doctor

Sun Protection Measures: Spending time in the sun increases your risk of skin cancer and early skin aging. To decrease this risk, regularly use a sunscreen with a Broad Spectrum SPF value of 15 or higher and other sun protection measures including:

• Limit time in the sun, especially from 10.00AM - 2.00PM

• Wear long-sleeved shirts, pants, hats, and sunglasses

Other Information:

• Protect this product from excess heat and direct sun.

• Store below 30°C / 86°F

Questions:

• info@nakedSundays.com